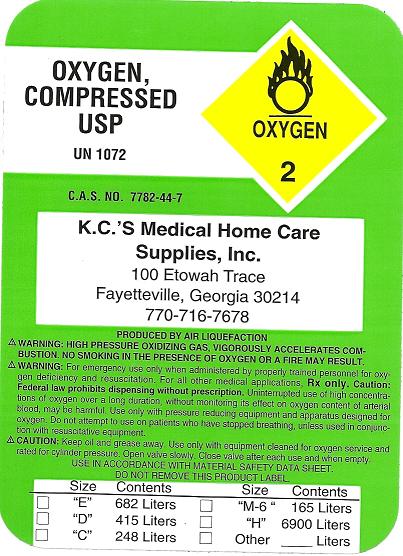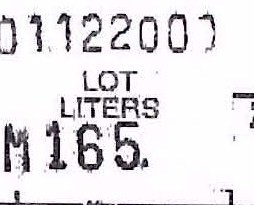 DRUG LABEL: Oxygen
NDC: 65676-0001 | Form: GAS
Manufacturer: KC's Medical Home Care Supplies, Inc. 
Category: prescription | Type: HUMAN PRESCRIPTION DRUG LABEL
Date: 20091224

ACTIVE INGREDIENTS: Oxygen 99 L/100 L

Oxygen